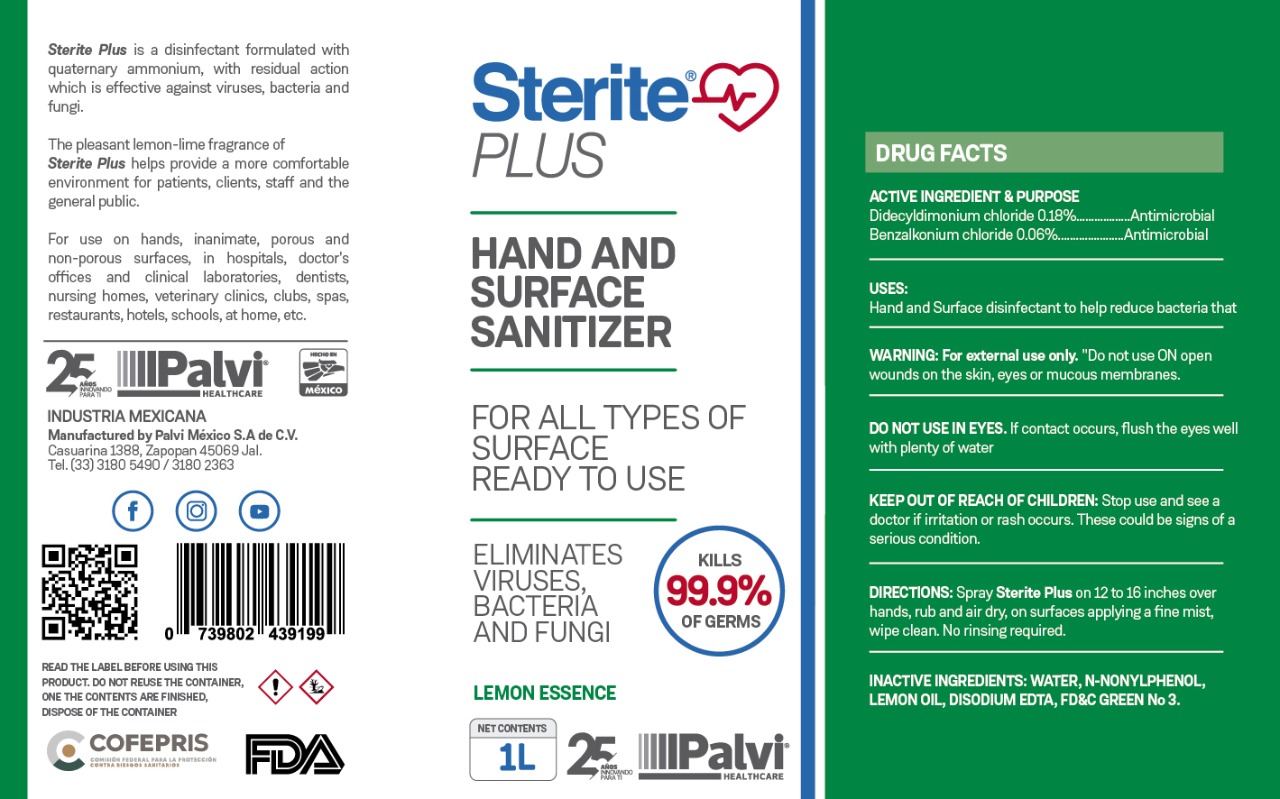 DRUG LABEL: STERITE PLUS
NDC: 81576-1000 | Form: LIQUID
Manufacturer: PALVI MEXICO, S.A. DE C.V.
Category: otc | Type: HUMAN OTC DRUG LABEL
Date: 20210216

ACTIVE INGREDIENTS: BENZALKONIUM CHLORIDE 0.0006 mg/1 mL; DIDECYLDIMONIUM CHLORIDE 0.0018 mg/1 mL
INACTIVE INGREDIENTS: EDETATE DISODIUM 0.0003 mL/1 mL; N-NONYLPHENOL (MIXED ISOMERS) 0.007 mL/1 mL; WATER 0.99 mL/1 mL; LEMON OIL 0.0002 mL/1 mL; ACID GREEN 50 0.0001 mL/1 mL

STERITE PLUS SANITIZER

ACTIVE INGREDIENTS

DIDECYLDIMONIUM CHLORIDE

BENZALKONIUM CHLORIDE

OTC PURPOSE SECTION

PURPOSE

ANTIMICROBIAL

INDICATIONS AND USAGE

HAND AND SURGACE DISINFECTANT TO HELP REDUCE BACTERIA THAT POTENTIALLY CAUSE DISEASES

DOSAGE AND ADMINISTRATION

DIRECTIONS SPRAY STERITE NEUTRUM ON 12 TO 16 INCHES OVER HANDS, RUB AND AIR DRY, ON SURFACES APPLYING A FINE MIST, WIPE CLEAN. NO RINSING REQUIRED.

WARNINGS AND PRECAUTIONS SECTION

DO NOT USE ON OPEN WOUNDS ON THE SKIN, EYES OR MUCOUS MEMBRANES

DO NOT USE IN EYES. IF CONTACT OCCURS, FLUSH THE EYES WELL WITH PLENTY OF WATER.

WARNINGS

WARNING FOR EXTERNAL USE ONLY

KEEP OUT OF REACH OF CHILDREN

INACTIVE INGREDIENT SECTION

INACTIVE INGREDIENTS: WATER, N-NONYLPHENOL, EUCALYPTOL, LEMON OIL, DISODIUM EDTA, FD&C GREEN NO.3